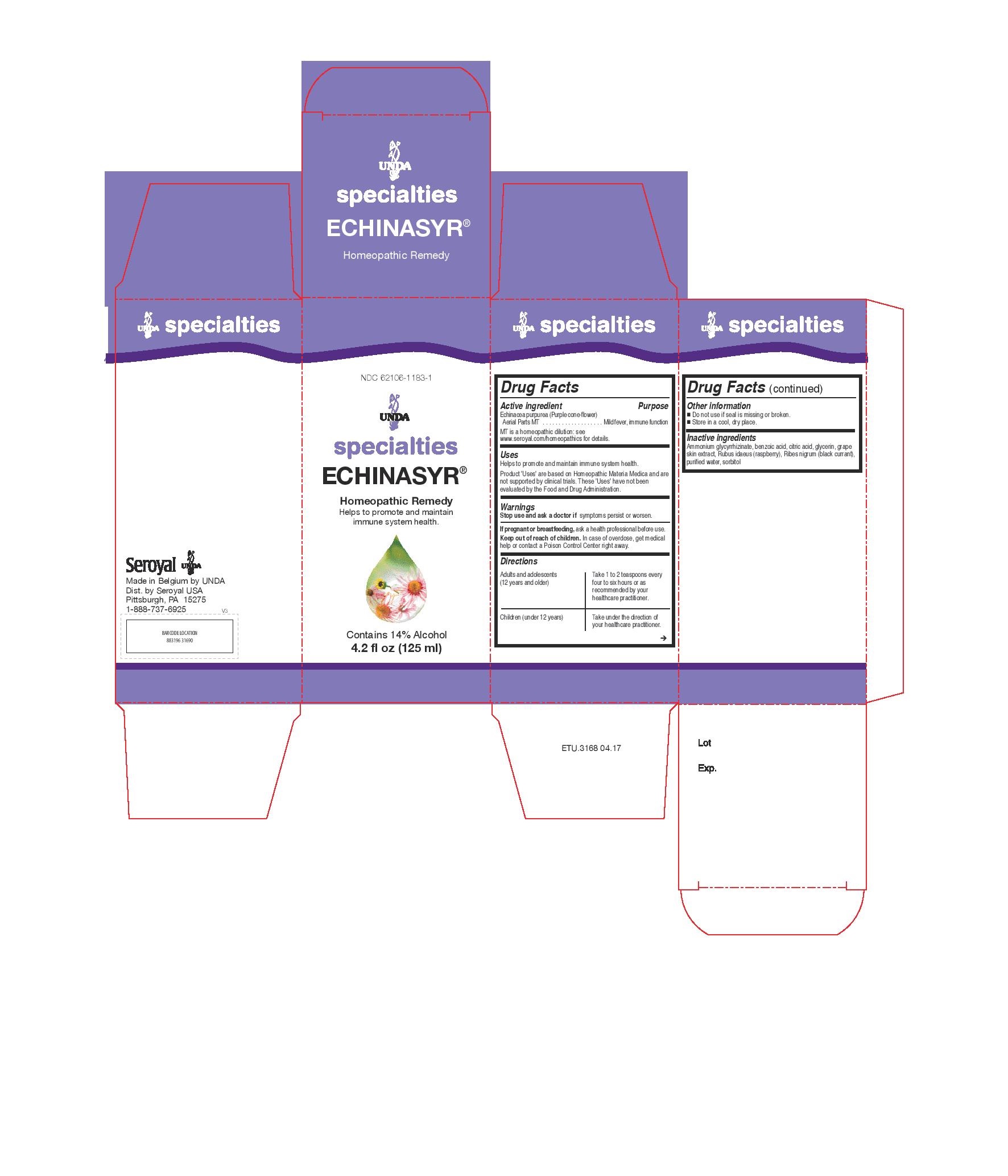 DRUG LABEL: ECHINASYR
NDC: 62106-1183 | Form: LIQUID
Manufacturer: Seroyal USA
Category: homeopathic | Type: HUMAN OTC DRUG LABEL
Date: 20221109

ACTIVE INGREDIENTS: ECHINACEA PURPUREA 18.125 g/125 mL
INACTIVE INGREDIENTS: SORBITOL; GLYCERIN; WATER; VITIS VINIFERA ANTHOCYANINS; BENZOIC ACID; AMMONIUM GLYCYRRHIZATE; RUBUS IDAEUS WHOLE; BLACK CURRANT; CITRIC ACID MONOHYDRATE

Echinasyr

Active ingredient
Echinacea purpurea (Purple cone-flower)
Aerial Parts MT

Uses
Helps to promote and maintain immune system health.

Warnings
Stop use and ask a doctor if symptoms persist or worsen.
If pregnant or breastfeeding, ask a health professional before use.
Keep out of reach of children. In case of overdose, get medical
help or contact a Poison Control Center right away.

Stop use and ask a doctor if symptoms persist or worsen.

PREGNANCY OR BREAST FEEDING

If pregnant or breastfeeding, ask a health professional before use.

Keep out of reach of children.

OVERDOSAGE

In case of overdose, get medical
help or contact a Poison Control Center right away.

Inactive ingredients
Ammonium glycyrrhizinate, benzoic acid, citric acid, glycerin, grape
skin extract, Rubus idaeus (raspberry), Ribes nigrum (black currant),
purified water, sorbitol

Directions

Adults and adolescents (12 years and older)

Take 1 to 2 teaspoons every four to six hours or as recommended by your healthcare practitioner.

Children (under 12 years)

Take under the direction of your healthcare practitioner.

Uses
Helps to promote and maintain immune system health.

Directions

Adults and adolescents (12 years and older)

Take 1 to 2 teaspoons every four to six hours or as recommended by your healthcare practitioner.

Children (under 12 years)

Take under the direction of your healthcare practitioner.

PACKAGE LABEL

NDC 62106-1183-1

UNDA

specialties

ECHINASYR®
Homeopathic Remedy

Helps to promote and maintain
immune system health.

Contains 14% Alcohol

4.2 fl oz (125 ml)